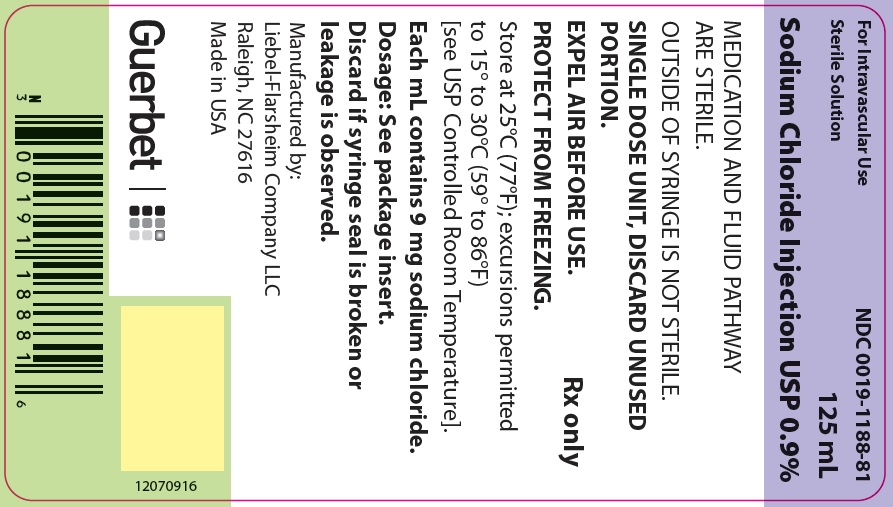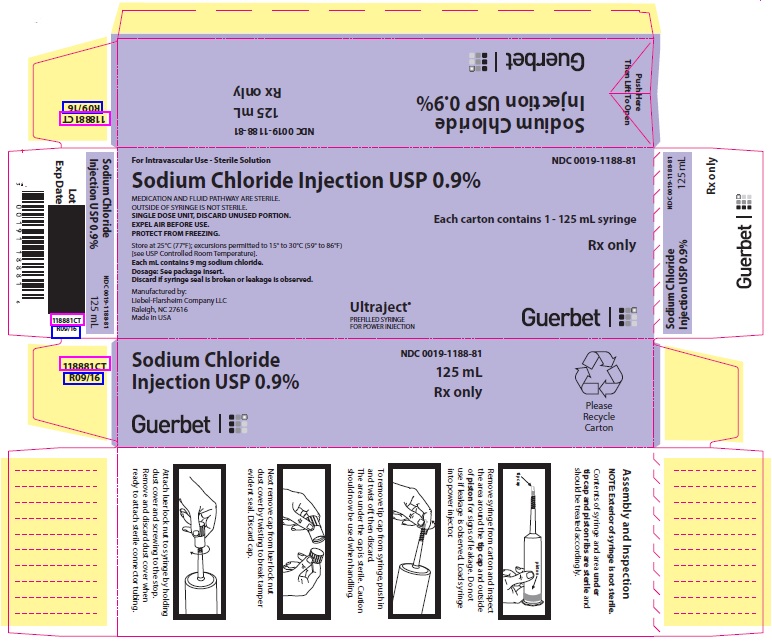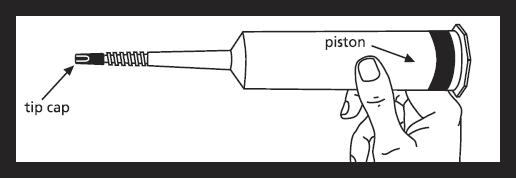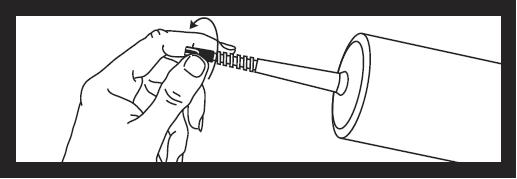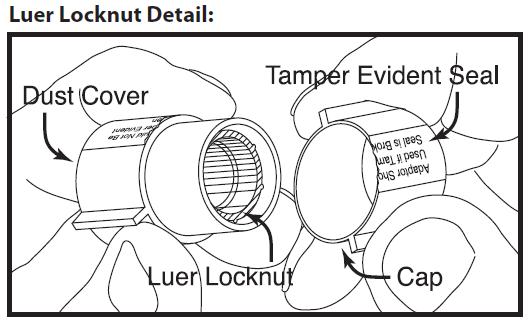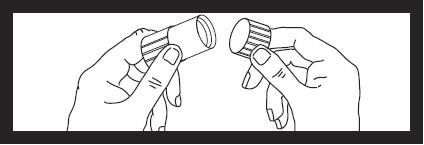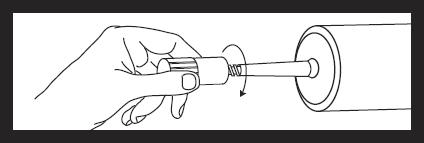 DRUG LABEL: SODIUM CHLORIDE
NDC: 0019-1188 | Form: INJECTION
Manufacturer: Liebel-Flarsheim Company LLC
Category: prescription | Type: HUMAN PRESCRIPTION DRUG LABEL
Date: 20221220

ACTIVE INGREDIENTS: SODIUM CHLORIDE .9 mg/1 mL
INACTIVE INGREDIENTS: WATER

HIGHLIGHTS OF PRESCRIBING INFORMATION

These highlights do not include all the information needed to use Sodium Chloride Injection USP 0.9% safely and effectively. See full prescribing information for Sodium Chloride Injection USP 0.9%.
Sodium Chloride Injection USP 0.9% Prefilled Syringes, For Intravascular Use Only
Initial U.S. Approval: 2006

1 INDICATIONS AND USAGE

- For use in flushing compatible contrast agents through Liebel-Flarsheim intravenous administration sets into indwelling intravascular access devices (1)

2 DOSAGE AND ADMINISTRATION

- For single patient use only. (2)
- Determine the volume of flush based on the imaging procedure, location of the vascular access device, length of tubing between power injector and vascular access device, and the contrast agent package insert. (2)
- Individualize the volume of flush based on body weight, fluid status and concomitant medical conditions. (2)
- Typical flush volumes for adults are 10 to 25 mL per injection at rates not to exceed 10 mL/sec. (2)
- May be used for additional infusion to maintain the patency of vascular access at a typical infusion rate of 0.5 to 1 mL per minute. (2)
- Do not use if packaging is damaged, wet, or not intact, if syringe or its tip cap shows signs of damage, leakage or displacement. Do not use if solution is hazy, cloudy, discolored, or contains particulate matter. (2)
- Use aseptic technique. (2)
- Expel residual air from the syringe and tubing prior to connection with the patient’s vascular access. (2)

3 DOSAGE FORMS AND STRENGTHS

- Supplied as a clear, colorless, odorless, sterile solution of Sodium Chloride 0.9% for intravenous administration (3)
- Supplied in 125 mL prefilled syringes (3)

4 CONTRAINDICATIONS

- None (4)

5 WARNINGS AND PRECAUTIONS

- Remove all air from the syringe and associated tubing prior to injection. (5.1)
- May cause fluid overload in patients with congestive heart failure, severe renal insufficiency, and in clinical states with edema, sodium retention, or hypernatremia. (5.3)
- Establish intravascular catheter patency prior to administration. (5.4)

6 ADVERSE REACTIONS

- Adverse reactions due to solution or administration technique may include: air embolism with stroke, chest pain, and dyspnea, arrhythmia, hypotension, myocardial infarction, sepsis, febrile response, local tenderness, infection at the site of injection, venous thrombosis or phlebitis extending from injection site, extravasation, fluid overload and hypervolemia. (6)

To report SUSPECTED ADVERSE REACTIONS, contact Liebel-Flarsheim Company LLC at 1-855-266-5037 or FDA at 1-800-FDA-1088 or www.fda.gov/medwatch.

8 USE IN SPECIFIC POPULATIONS

- Pregnancy: It is not known whether Sodium Chloride Injection USP 0.9% can cause fetal harm. (8.1)
- Pediatrics: Safety and effectiveness have not been established in pediatric patients. (8.4)
- Geriatrics: Dosing for an elderly patient should be cautious, reflecting the greater frequency of decreased hepatic, renal, or cardiac function, and of concomitant disease or other drug therapy. (8.5)

FULL PRESCRIBING INFORMATION

1 INDICATIONS AND USAGE

- 125 mL Syringe: Sodium Chloride Injection USP 0.9% is indicated for use in flushing compatible contrast agents through Liebel-Flarsheim intravenous administration sets into indwelling intravascular access devices only when delivered by the following Liebel-Flarsheim power injectors: Angiomat®, Illumena®, Illumena® Néo, CT9000®, CT9000® ADV, Optistat®, Optivantage® and Optistar Elite.

2 DOSAGE AND ADMINISTRATION

- The 125 mL syringe are for single patient use only.
- Determine the volume of the saline flush for each patient individually based, in part, on the imaging procedure, the location of the vascular access device, the length of tubing between the Liebel-Flarsheim contrast agent power injector and the vascular access device and the recommendations made on the package insert for the contrast agent. Typical Sodium Chloride Injection USP 0.9% flush volumes following contrast agent administration in adults are 10 to 25 mL per injection at rates not to exceed 10 mL/sec.
- Use of some Liebel-Flarsheim contrast agent power injectors allows for additional infusion of Sodium Chloride Injection USP 0.9% to maintain the patency of vascular access. Typical infusion rates used for this purpose are in the range of 0.5 to 1 mL per minute.
- Individualize infusion rates and flush volumes for each patient based on their body weight, fluid status and concomitant medical conditions.
- Consult the Liebel-Flarsheim contrast agent power injector manual for proper use.

2.1 Drug Handling

- Inspect the syringe for signs of break in sterility.
- Do not use if the syringe or its tip cap shows signs of damage, leakage or displacement.
- Do not use if the solution is hazy, cloudy, discolored or contains particulate matter.
- Use aseptic technique.
- Expel residual air in both the syringe and tubing prior to connection with the patient’s vascular access.
- Instructions for assembly and inspection of the Sodium Chloride Injection USP 0.9% syringes prior to use are printed on this sheet.

2.2 125 mL Syringe Assembly and Inspection

NOTE: Exterior of syringe is not sterile.
Contents of syringe and area under tip cap and piston ribs are sterile and should be treated accordingly.

Remove syringe from carton and inspect the area around the tip cap and outside of piston for signs of leakage. Do not use if leakage is observed. Load syringe into power injector.

To remove tip cap from syringe, push in and twist off, then discard.
The area under the cap is sterile. Caution should now be used when handling.

Next remove cap from luer locknut dust cover by twisting to break tamper evident seal. Discard cap.

Attach luer locknut to syringe by holding dust cover and screwing to the stop.
Remove and discard dust cover when ready to attach sterile connector tubing.

3 DOSAGE FORMS AND STRENGTHS

Sodium Chloride Injection USP (0.9%)

- a clear, colorless, odorless solution
- supplied in 125 mL prefilled syringes
- contents are sterile

4 CONTRAINDICATIONS

None

5 WARNINGS AND PRECAUTIONS

5.1 Air Embolism

Remove all air from the syringe and associated tubing prior to injection to avoid air embolus with the associated risk of stroke, organ ischemia and/or infarction, and death.

5.2 Infectious Complications

Use of a damaged syringe or failure to maintain aseptic technique may result in infection, sepsis and death [see Dosage and Administration (2)].

5.3 Fluid Overload

Sodium Chloride Injection USP 0.9% may cause fluid overload in patients with congestive heart failure, severe renal insufficiency, and in clinical states with edema, sodium retention, or hypernatremia.

Consider each patient’s age, body weight, fluid status, concomitant medical conditions and planned radiological procedure to determine if use of Sodium Chloride Injection USP 0.9% is appropriate.

5.4 Extravasation

Extravasation of the Sodium Chloride Injection USP 0.9% may cause mechanical compression of neurovascular structures. Extravasation of contrast agent may result in tissue injury by osmolar and direct cytotoxicity (see package inserts of specific contrast agents). Establish intravascular catheter patency prior to the administration of Sodium Chloride Injection USP 0.9%.

6 ADVERSE REACTIONS

Reported adverse reactions include:

- air embolization with stroke, chest pain, and dyspnea
- arrhythmia
- hypotension
- myocardial infarction
- sepsis
- febrile response
- local tenderness
- infection at the site of injection
- venous thrombosis or phlebitis extending from injection site
- extravasation
- fluid overload
- hypervolemia

8 USE IN SPECIFIC POPULATIONS

8.1 Pregnancy

Risk Summary
Administration of Sodium Chloride Injection USP 0.9% is not known to cause major birth defects, miscarriage or adverse maternal or fetal outcomes. Animal reproduction studies have not been conducted with Sodium Chloride Injection USP 0.9.%

All pregnancies have a background risk of birth defect, loss, or other adverse outcomes. In the U.S. general population, the estimated background risk of major birth defects and miscarriage in clinically recognized pregnancies is 2-4% and 15-20%, respectively.

8.2 Lactation

Risk Summary
Appropriate administration of Sodium Chloride Injection USP 0.9% is not known to cause harm to a breastfed infant.

8.4 Pediatric Use

Safety and effectiveness of Sodium Chloride Injection USP 0.9% administered by power injection in pediatric patients have not been established. Administration of Sodium Chloride Injection USP 0.9% to pediatric patients by power injection is not recommended. When performing manual injection of Sodium Chloride Injection USP 0.9% to pediatric patients, take into account the patient’s weight, fluid status, and concomitant medical conditions to determine if use of Sodium Chloride Injection USP 0.9% is appropriate.
The safety of manual injection of Sodium Chloride Injection USP 0.9% in pediatric patients is supported by reported clinical experience with intravenous infusion and flush of sodium chloride injection in pediatric patients.
To minimize the risk of fluid overload, use the smallest dose of Sodium Chloride Injection USP 0.9% necessary for manually flushing contrast agent through the vascular access line.

8.5 Geriatric Use

No clinical studies of Sodium Chloride Injection USP 0.9% were conducted. Other reported clinical experience with sodium chloride injection has not identified differences in responses between the elderly and younger patients. In general, dose selection for an elderly patient should be cautious, usually starting at the low end of the dosing range, reflecting the greater frequency of decreased hepatic, renal, or cardiac function, and of concomitant disease or other drug therapy.

10 OVERDOSAGE

Use of Sodium Chloride Injection USP 0.9% may pose a threat of overdose marked by electrolyte disturbance and/or fluid overload, particularly in pediatric patients and patients with compromised renal or cardiac function. In the event of overdosage, discontinue the infusion, reevaluate the patient and institute appropriate corrective action.

11 DESCRIPTION

Sodium Chloride Injection USP 0.9% is a formulation of sodium chloride in Water for Intravascular Injection. No preservative, antimicrobial agent or buffer is added. Sodium Chloride Injection USP 0.9% is provided as a sterile, nonpyrogenic, clear, colorless, odorless solution.
Molecular formula = NaCl MW = 58.44
Each mL of Sodium Chloride Injection USP 0.9% contains 9 mg of sodium chloride. The pH is 4.5 to 7.0. The osmolarity is 308 mOsm/L (calc.).
Sodium Chloride Injection USP 0.9% is provided in a 125 mL syringe with a 125 mL fill. The syringes are for single patient use and are disposable and not meant for reuse.

12 CLINICAL PHARMACOLOGY

Sodium Chloride Injection USP 0.9% has an osmotic pressure similar to plasma.

16 HOW SUPPLIED/STORAGE AND HANDLING

Sodium Chloride Injection USP 0.9% is a clear, colorless, odorless solution containing 9 mg/mL of sodium chloride. Sodium Chloride Injection USP 0.9% is supplied in 125 mL prefilled syringes containing 125 mL of solution. Each syringe is sealed with rubber closures and the contents are sterile. The 125 mL syringe is supplied with a luer locknut adapter which is cleared for manufacture and distribution as a device under 510(K) number 862653. The syringes are contained in shipping cartons with the following configurations:

Volume | Packaging | NDC
125 mL in plastic syringes | 20 syringes per carton | 0019-1188-81
125 mL in plastic RFID-Tagged Syringes* | 20 syringes per carton | 0019-1188-27
*Radio Frequency Identification (RFID) Technology

RFID-Tagged Syringe Description

This information is for Ultraject® syringes containing Sodium Chloride Injection USP 0.9% that has been labeled with a Radio Frequency Identification (RFID) tag. When used with an RFID-enabled Optivantage Injector, this tag allows for the exchange of product information such as lot number, expiration, concentration, and identification of the syringe as being unused prior to use and used after product administration. Patient information is not utilized in any form with this RFID technology. Sodium Chloride Injection USP 0.9% product quality is not impacted with the use of this RFID tag. Sodium Chloride Injection USP 0.9% RFID syringes require no special handling and should be stored at the conditions listed for the drug product.

RFID-Tagged Syringe Directions for Use

For the RFID technology to function, the syringe must be used with an Optivantage Injector with RFID technology. Function of the RFID technology is not dependent on syringe orientation as it is placed in the injector. Instructions for use of the injector are provided on the injector interface screens and operator’s manual.

If the RFID tag is damaged or otherwise non-functional, the injector will notify the user. Should this occur, the Sodium Chloride Injection USP 0.9% syringe with the non-functional RFID tag may still be used but no data will be transferred to the injector.

Regarding interference with medical devices, the RFID tag and injector system meet the IEC 60601-1-2 requirements for emission and immunity standards for medical devices. Follow all manufacturers’ guidelines and do not operate any part of the Optivantage Injector System and RFID-tagged syringes within 6 inches (15 cm) of a pacemaker and/or defibrillator.

Storage

Store Sodium Chloride Injection USP 0.9% syringes and RFID-tagged syringes at 25°C (77°F); excursions permitted to 15° to 30°C (59° to 86°F) [see USP Controlled Room Temperature].

PROTECT FROM FREEZING

Manufactured by:
Liebel-Flarsheim Company LLC
Raleigh, NC 27616

Made in USA

GBT 11880919

Issued: 9/19

Guerbet

PACKAGE LABEL - PRINCIPAL DISPLAY PANEL - 125 mL Syringe

For Intravascular Use

Sterile Solution

NDC 0019-1188-81

125 mL

Sodium Chloride Injection USP 0.9%

MEDICATION AND FLUID PATHWAY ARE STERILE.
OUTSIDE OF SYRINGE IS NOT STERILE.

SINGLE DOSE UNIT, DISCARD UNUSED PORTION.
EXPEL AIR BEFORE USE.
PROTECT FROM FREEZING.

Rx only

Store at 25°C (77°F); excursions permitted to 15° to 30°C (59° to 86°F) [see USP Controlled Room Temperature].

Each mL contains 9 mg sodium chloride.
Dosage: See package insert.
Discard if syringe seal is broken or leakage is observed.

Manufactured by:Liebel-Flarsheim Company LLC
Raleigh, NC 27616
Made in USA

Guerbet

12070916